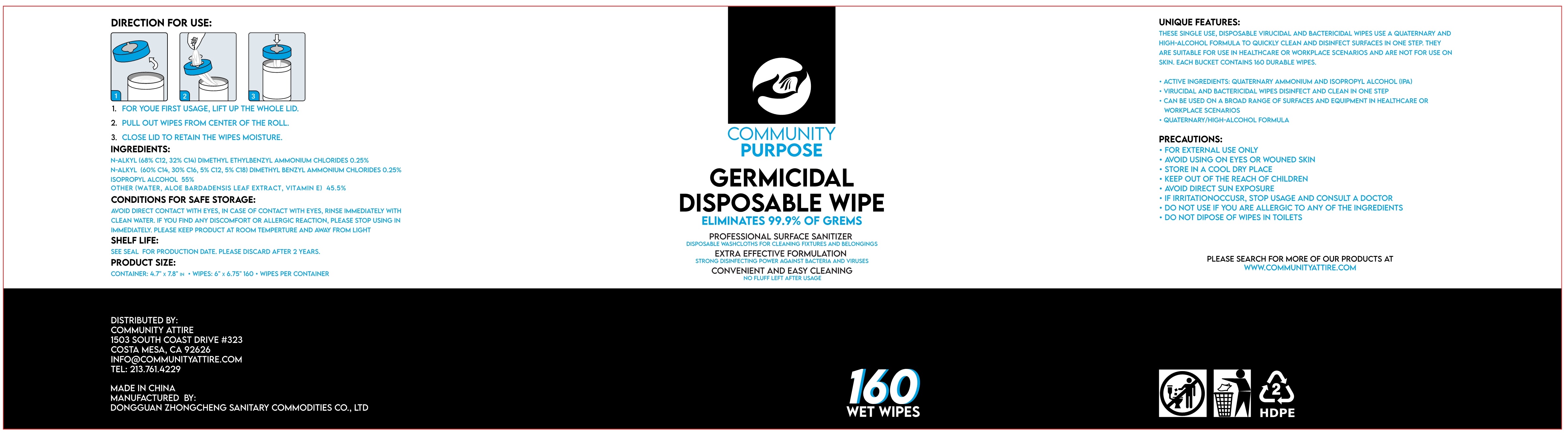 DRUG LABEL: GERMICIDAL DISPOSABLE WIPE
NDC: 55482-160 | Form: CLOTH
Manufacturer: Dongguan Zhongcheng Sanitary Commodities Co., Ltd.
Category: otc | Type: HUMAN OTC DRUG LABEL
Date: 20200804

ACTIVE INGREDIENTS: ISOPROPYL ALCOHOL 55 mL/100 1; N-ALKYL ETHYLBENZYL DIMETHYL AMMONIUM CHLORIDE (C12-C14) 0.25 g/100 1; N-ALKYL ETHYLBENZYL DIMETHYL AMMONIUM (C12-C14) 0.25 g/100 1
INACTIVE INGREDIENTS: .ALPHA.-TOCOPHEROL; ALOE; WATER

55482-160 DISINFECTING WIPES

Active Ingredient(s)

ISOPROPYL ALCOHOL , N-ALKYL DIMETYL ETHYLBENZYL AMMONIUM CHLORIDES,N-ALKYL DIMETHYL BENZYL BENZYL AMMONIUM CHLORIDES, Purpose: Antiseptic

Purpose

Antiseptic,Wipes

Use

1.FOR YOUE FIRST USAGE, LIFT UP THE WHOLE LID.

2.PULL OUT WIPES FROM CENTER OF THE ROLL.

3.CLOSE LID TO RETAIN THE WIPES MOISTURE.

Warnings

- FOR EXTERNAL USE ONLY.
  - AVOID USING ON EYES OR WOUNED SKIN.
  - STORE IN A COOL DRY PLACE.
  - KEEP OUT OF THE REACH OF CHILDREN.
  - AVOID DIRECT SUN EXPOSURE.
  - IF IRRITATIONOCCUSR ,STOP USAGE AND CONSULT A DOCTOR.
  - DO NOT USE IF YOU ARE ALLERGIC TO ANY OF THE INGREDIENTS.
  - DO NOT DIPOSE OF WIPES IN TOILETS.

Do not use

- IF YOU ARE ALLERGIC TO ANY OF THE INGREDIENTS

When using this product keep out of eyes, ears, and mouth. In case of contact with eyes, rinse eyes thoroughly with water.
Stop use and ask a doctor if irritation or rash occurs. These may be signs of a serious condition.
Keep out of reach of children. If swallowed, get medical help or contact a Poison Control Center right away.

Stop use and ask a doctor if irritation or rash occurs. These may be signs of a serious condition.

Keep out of reach of children. If swallowed, get medical help or contact a Poison Control Center right away.

Directions

- THESE SINGLE USE ,DISPOSABLE VIRUCIDAL AND BACTERICIDAL WIPES USE A QUATERNARY AND HIGH-ALCOHOL FORMULA TO QUICKLY CLEAN AND DISINFECT SURFACES IN ONE STEP . THEY ARE SUITABLE FOR USE IN HEALTHCARE OR WORKPLACE SCENARIOS AND ARE NOT FOR USE ON SKIN .EACH BUCKET CONTAINS 160 DURABLE WIPES.
- ACTIVE INGREDIENTS: QUATERNARY AMMONIUM AND ISOPROPYL ALCOHOL(IPA)
- VIRUCIDAL AND BACTERICIDAL WIPES DISINFECT AND CLEAN IN ONE STEP
- CAN BE USED ON A BROAD RANGE OF SURFACES AND EQUIPMENT IN HEALTHCARE OR WORKPLACE SCENARIOS
- QUATERNARY/HIGH-ALCOHOL FORMULA

Other information

- AVOID DIRECT CONTACT WITH EYES.IN CASE OF CONTACT WITH EYES,RINSE IMMEDIATELY WITH CLEAN WATER.
- IF YOU FIND ANY DISCOMFORT OR ALLERGIC REACTION,PLEASE STOP USING IN IMMEDIATELY.
- PLEASE KEEP PRODUCT AT ROOM TEMPERTURE AND AWAY FROM LIGHT.
- SEE SEAL FOR PRODUCTION DATE. PLEASE DISCARD AFTER 2 YEARS.

Inactive ingredients

WATER,ALOE BARDADENSIS LEAF EXTRACT, VITAMIN E.

Package Label - Principal Display Panel

160 CLOTH NDC:55482-160-01